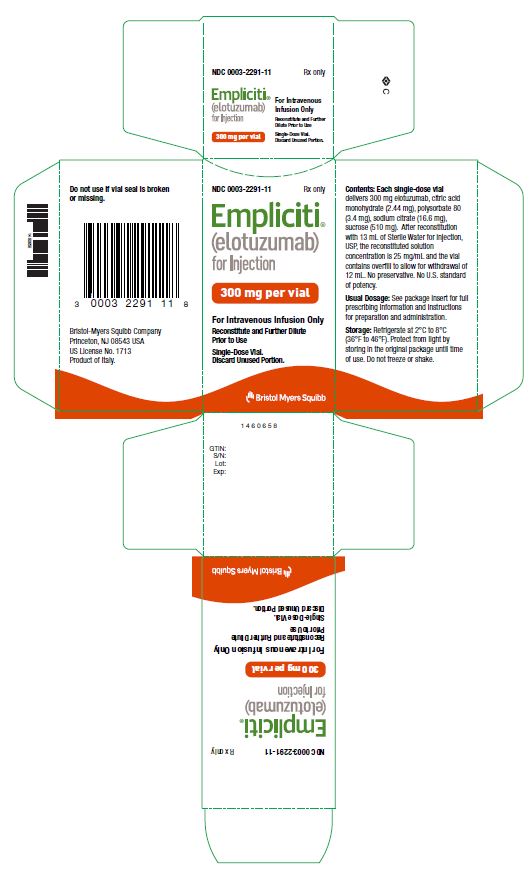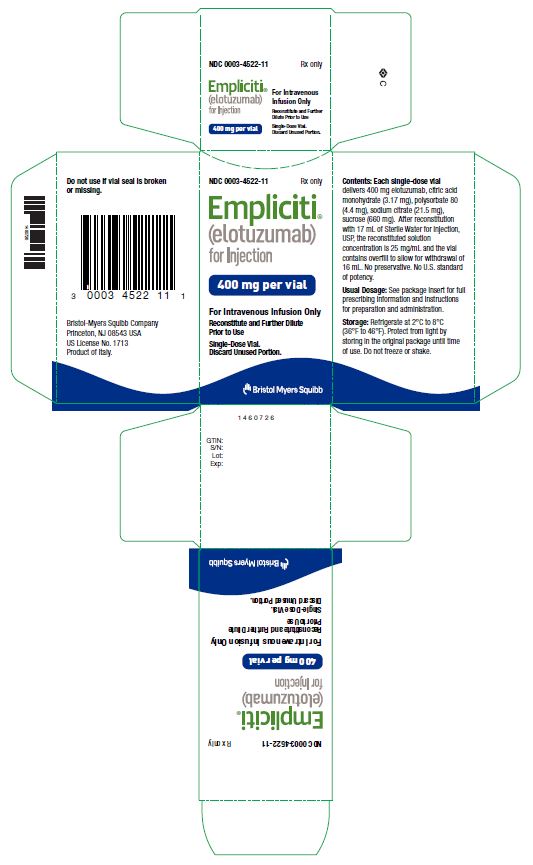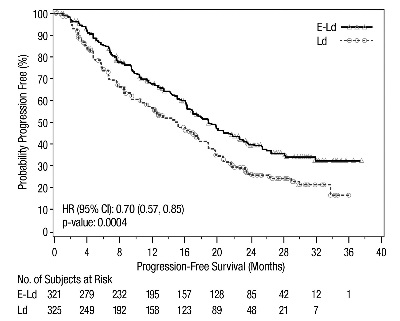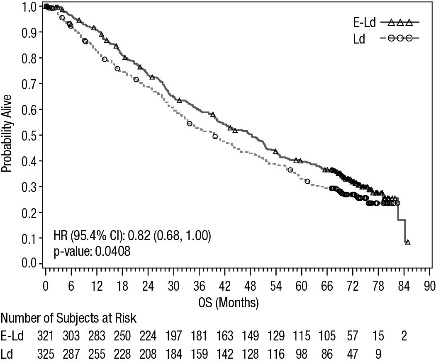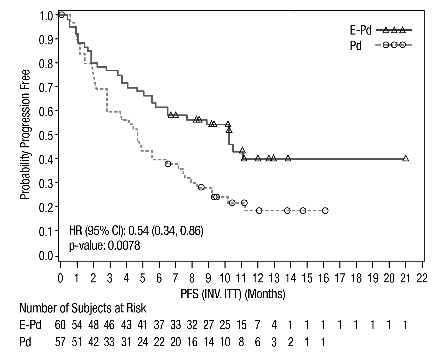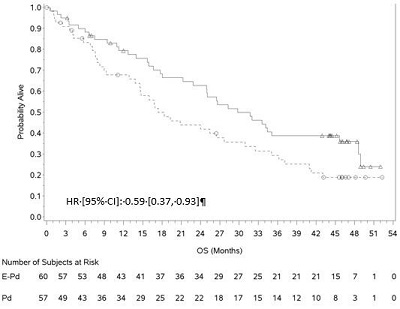 DRUG LABEL: EMPLICITI
NDC: 0003-2291 | Form: INJECTION, POWDER, LYOPHILIZED, FOR SOLUTION
Manufacturer: E.R. Squibb & Sons, L.L.C.
Category: prescription | Type: HUMAN PRESCRIPTION DRUG LABEL
Date: 20220322

ACTIVE INGREDIENTS: ELOTUZUMAB 300 mg/1 1
INACTIVE INGREDIENTS: CITRIC ACID MONOHYDRATE 2.44 mg/1 1; POLYSORBATE 80 3.4 mg/1 1; SODIUM CITRATE, UNSPECIFIED FORM 16.6 mg/1 1; SUCROSE 510 mg/1 1

HIGHLIGHTS OF PRESCRIBING INFORMATION

These highlights do not include all the information needed to use EMPLICITI safely and effectively. See full prescribing information for EMPLICITI.
EMPLICITI® (elotuzumab) for injection, for intravenous use
Initial U.S. Approval: 2015

1 INDICATIONS AND USAGE

EMPLICITI is a SLAMF7-directed immunostimulatory antibody indicated in

- combination with lenalidomide and dexamethasone for the treatment of adult patients with multiple myeloma who have received one to three prior therapies. (1)
- combination with pomalidomide and dexamethasone for the treatment of adult patients with multiple myeloma who have received at least two prior therapies including lenalidomide and a proteasome inhibitor. (1)

2 DOSAGE AND ADMINISTRATION

- With lenalidomide and dexamethasone: 10 mg/kg administered intravenously every week for the first two cycles and every 2 weeks thereafter until disease progression or unacceptable toxicity. (2.1)
- With pomalidomide and dexamethasone: 10 mg/kg administered intravenously every week for the first two cycles and 20 mg/kg every 4 weeks thereafter until disease progression or unacceptable toxicity. (2.2)
- Premedicate with dexamethasone, diphenhydramine, ranitidine and acetaminophen. (2.3)

3 DOSAGE FORMS AND STRENGTHS

For Injection: 300 mg or 400 mg lyophilized powder in a single-dose vial for reconstitution. (3)

4 CONTRAINDICATIONS

None (4)

5 WARNINGS AND PRECAUTIONS

- Infusion reactions: Premedication is required. Interrupt EMPLICITI for Grade 2 or higher and permanently discontinue for severe infusion reaction. (2.3, 2.4, 5.1)
- Infections: Monitor for fever and other signs of infection and treat promptly. (5.2)
- Second Primary Malignancies (SPM): Higher incidences of SPM were observed in a controlled clinical trial of patients with multiple myeloma receiving EMPLICITI. (5.3)
- Hepatotoxicity: Monitor liver function and stop EMPLICITI if hepatotoxicity is suspected. (5.4)
- Interference with determination of complete response: EMPLICITI can interfere with assays used to monitor M-protein. This interference can impact the determination of complete response. (5.5)

6 ADVERSE REACTIONS

Most common adverse reactions (20% or higher)

- with lenalidomide and dexamethasone are fatigue, diarrhea, pyrexia, constipation, cough, peripheral neuropathy, nasopharyngitis, upper respiratory tract infection, decreased appetite, pneumonia. (6.1)
- with pomalidomide and dexamethasone are constipation and hyperglycemia. (6.1)

To report SUSPECTED ADVERSE REACTIONS, contact Bristol-Myers Squibb at 1-800-721-5072 or FDA at 1-800-FDA-1088 or www.fda.gov/medwatch.

8 USE IN SPECIFIC POPULATIONS

Pregnancy: Embryo-fetal toxicity in combination with lenalidomide and dexamethasone or pomalidomide and dexamethasone. (8.1)

FULL PRESCRIBING INFORMATION

1 INDICATIONS AND USAGE

- EMPLICITI is indicated in combination with lenalidomide and dexamethasone for the treatment of adult patients with multiple myeloma who have received one to three prior therapies.
- EMPLICITI is indicated in combination with pomalidomide and dexamethasone for the treatment of adult patients with multiple myeloma who have received at least two prior therapies including lenalidomide and a proteasome inhibitor.

2 DOSAGE AND ADMINISTRATION

2.1 Recommended Dosing when EMPLICITI Is Used in Combination with Lenalidomide and Dexamethasone

The recommended dosage of EMPLICITI is 10 mg/kg administered intravenously every week for the first two cycles (28-day cycle) and every 2 weeks thereafter in conjunction with the recommended dosing of lenalidomide and low-dose dexamethasone as described below. Continue treatment until disease progression or unacceptable toxicity.

Refer to the dexamethasone and lenalidomide prescribing information for additional information.

Administer premedications before each dose of EMPLICITI [see Dosage and Administration (2.3) and Warnings and Precautions (5.1)].

Administer dexamethasone as follows:

- On days that EMPLICITI is administered, give dexamethasone 28 mg orally between 3 and 24 hours before EMPLICITI plus 8 mg intravenously between 45 and 90 minutes before EMPLICITI.
- On days that EMPLICITI is not administered but a dose of dexamethasone is scheduled (Days 8 and 22 of cycle 3 and all subsequent cycles), give 40 mg orally.

The recommended dosing is presented in Table 1.

Table 1: Recommended Dosing Schedule of EMPLICITI in Combination with Lenalidomide and Dexamethasone
Cycle | 28-Day Cycles 1 and 2 |  |  |  | 28-Day Cycles 3+
Day of Cycle | 1 | 8 | 15 | 22 | 1 | 8 | 15 | 22
Premedication* | ✓ | ✓ | ✓ | ✓ | ✓ |  | ✓
EMPLICITI (mg/kg) intravenously | 10 | 10 | 10 | 10 | 10 |  | 10
Lenalidomide (25 mg) orally | Days 1-21 |  |  |  | Days 1-21
Dexamethasone† (mg) orally | 28 | 28 | 28 | 28 | 28 | 40 | 28 | 40
Dexamethasone** (mg) intravenously | 8 | 8 | 8 | 8 | 8 |  | 8
Day of Cycle | 1 | 8 | 15 | 22 | 1 | 8 | 15 | 22
* Premedicate with the following 45 to 90 minutes prior to EMPLICITI infusion: 8 mg intravenous dexamethasone, H1 blocker: diphenhydramine (25 to 50 mg orally or intravenously) or equivalent; H2 blocker: ranitidine (50 mg intravenously) or equivalent; acetaminophen (650 to 1000 mg orally).
† Oral dexamethasone (28 mg) taken between 3 and 24 hours before EMPLICITI infusion.
** Intravenous dexamethasone 45-90 minutes before EMPLICITI infusion.

2.2 Recommended Dosing when EMPLICITI Is Used in Combination with Pomalidomide and Dexamethasone

The recommended dosage of EMPLICITI is 10 mg/kg administered intravenously every week for the first two cycles (28-day cycle). Starting at cycle 3 (28-day cycle), administer EMPLICITI 20 mg/kg intravenously every 4 weeks. Administer EMPLICITI in conjunction with pomalidomide and low-dose dexamethasone as described below (Table 2). Continue treatment until disease progression or unacceptable toxicity.

Refer to the dexamethasone and pomalidomide prescribing information for additional information.

Administer premedications before each dose of EMPLICITI [see Dosage and Administration (2.3) and Warnings and Precautions (5.1)].

Administer dexamethasone as follows:

- On days that EMPLICITI is administered, for patients 75 years or younger give dexamethasone 28 mg orally between 3 and 24 hours before EMPLICITI plus 8 mg intravenously between 45 and 90 minutes before EMPLICITI and for patients older than 75 years give dexamethasone 8 mg orally between 3 and 24 hours before EMPLICITI plus 8 mg intravenously between 45 and 90 minutes before EMPLICITI.
- On days that EMPLICITI is not administered but a dose of dexamethasone is scheduled (Days 8, 15 and 22 of cycle 3 and all subsequent cycles), give 40 mg orally to patients 75 years or younger and 20 mg orally to patients older than 75 years.

The recommended dosing is presented in Table 2.

Table 2: Recommended Dosing Schedule of EMPLICITI in Combination with Pomalidomide and Dexamethasone
Cycle | 28-Day Cycles 1 and 2 |  |  |  | 28-Day Cycles 3+
Day of Cycle | 1 | 8 | 15 | 22 | 1 | 8 | 15 | 22
Premedication* | ✓ | ✓ | ✓ | ✓ | ✓
EMPLICITI (mg/kg) intravenously | 10 | 10 | 10 | 10 | 20
Pomalidomide (4 mg) orally | Days 1-21 |  |  |  | Days 1-21
Dexamethasone† (mg) orally ≤75 years old | 28 | 28 | 28 | 28 | 28 | 40 | 40 | 40
Dexamethasone† (mg) orally >75 years old | 8 | 8 | 8 | 8 | 8 | 20 | 20 | 20
Dexamethasone** (mg) intravenously | 8 | 8 | 8 | 8 | 8
* Premedicate with the following 45 to 90 minutes prior to EMPLICITI infusion: 8 mg intravenous dexamethasone, H1 blocker: diphenhydramine (25 to 50 mg orally or intravenously) or equivalent; H2 blocker: ranitidine (50 mg intravenously) or equivalent; acetaminophen (650 to 1000 mg orally).
† Oral dexamethasone taken between 3 and 24 hours before EMPLICITI infusion.
** Intravenous dexamethasone 45-90 minutes before EMPLICITI infusion.

2.3 Premedication

Dexamethasone

When EMPLICITI is used in combination with lenalidomide or pomalidomide and dexamethasone, divide dexamethasone into an oral and intravenous dose and administer as shown in Table 1 and Table 2 [see Dosage and Administration (2.1, 2.2)].

Other Medications

In addition to dexamethasone, complete administration of the following medications 45 to 90 minutes prior to EMPLICITI infusion:

- H1 blocker: diphenhydramine (25 to 50 mg orally or intravenously) or equivalent H1 blocker.
- H2 blocker: ranitidine (50 mg intravenously or 150 mg orally) or equivalent H2 blocker.
- Acetaminophen (650 to 1000 mg orally).

2.4 Dose Modifications

If the dose of one drug in the regimen is delayed, interrupted, or discontinued, the treatment with the other drugs may continue as scheduled. However, if dexamethasone is delayed or discontinued, base the decision whether to administer EMPLICITI on clinical judgment (i.e., risk of hypersensitivity).

If a Grade 2 or higher infusion reaction occurs during EMPLICITI administration, interrupt the infusion and institute appropriate medical and supportive measures. Upon resolution to Grade 1 or lower, restart EMPLICITI at 0.5 mL per minute and gradually increase at a rate of 0.5 mL per minute every 30 minutes as tolerated to the rate at which the infusion reaction occurred. Resume the escalation regimen if there is no recurrence of the infusion reaction (see Table 3 and Table 4).

In patients who experience an infusion reaction, monitor vital signs every 30 minutes for 2 hours after the end of the EMPLICITI infusion. If the infusion reaction recurs, stop the EMPLICITI infusion and do not restart on that day [see Warnings and Precautions (5.1)]. Severe infusion reactions may require permanent discontinuation of EMPLICITI therapy and emergency treatment.

Dose delays and modifications for dexamethasone, pomalidomide and lenalidomide should be performed as recommended in their Prescribing Information.

2.5 Administration

Administer the entire EMPLICITI infusion with an infusion set and a sterile, nonpyrogenic, low-protein-binding filter (with a pore size of 0.2 to 1.2 micrometer) using an automated infusion pump.

Initiate EMPLICITI infusion at a rate of 0.5 mL per minute for 10 mg/kg dose. The infusion rate may be increased in a stepwise fashion as described in Table 3 if no infusion reactions develop. The maximum infusion rate should not exceed 5 mL per minute.

Table 3: Infusion Rate for EMPLICITI 10 mg/kg
Cycle 1, Dose 1 |  | Cycle 1, Dose 2 |  | Cycle 1, Dose 3 and 4 and All Subsequent Cycles
Time Interval | Rate | Time Interval | Rate | Rate
0-30 min | 0.5 mL/min | 0-30 min | 3 mL/min
30-60 min | 1 mL/min | 30 min or more | 4 mL/min | 5 mL/min
60 min or more | 2 mL/min | - | -

Initiate EMPLICITI infusion rate at 3 mL per minute for 20 mg/kg dose. The infusion rate may be increased in a stepwise fashion as described in Table 4 if no infusion reactions develop. The maximum infusion rate should not exceed 5 mL per minute.

Patients who have escalated to 5 mL/min at 10 mg/kg dose must decrease the rate to 3 mL/min at the first infusion at 20 mg/kg.

Table 4: Infusion Rate for EMPLICITI 20 mg/kg
Dose 1 |  | Dose 2 and all subsequent doses
Time Interval | Rate | Rate
0-30 min | 3 mL/min
30 min or more | 4 mL/min | 5 mL/min

Adjust the infusion rate following a Grade 2 or higher infusion reaction [see Dosage and Administration (2.4)].

Do not mix EMPLICITI with, or administer as an infusion with, other medicinal products. No physical or biochemical compatibility studies have been conducted to evaluate the coadministration of EMPLICITI with other agents.

2.6 Reconstitution and Preparation

Calculation of Dose

- Calculate the dose (mg) and determine the number of vials needed for the 10 mg/kg and 20 mg/kg dosage based on patient weight.
- Determine the volume of sterile water for injection (SWFI) needed for reconstitution as shown in Table 5.

Table 5: Reconstitution Instructions for EMPLICITI
Strength | Amount of Sterile Water for Injection, USP Required for Reconstitution | Deliverable Volume of Reconstituted EMPLICITI in the Vial | Postreconstitution Concentration
300 mg vial | 13 mL | 12 mL* | 25 mg/mL
400 mg vial | 17 mL | 16 mL* | 25 mg/mL
* After reconstitution, each vial contains overfill to allow for withdrawal of 12 mL (300 mg) and 16 mL (400 mg), respectively.

Reconstitution

- Aseptically reconstitute each EMPLICITI vial with a syringe of adequate size and a less than or equal to 18-gauge needle (e.g., 17-gauge). A slight back pressure may be experienced during administration of the Sterile Water for Injection, USP, which is considered normal.
- Hold the vial upright and swirl the solution by rotating the vial to dissolve the lyophilized cake. Invert the vial a few times in order to dissolve any powder that may be present on top of the vial or the stopper. Avoid vigorous agitation. DO NOT SHAKE. The lyophilized powder should dissolve in less than 10 minutes.
- After the remaining solids are completely dissolved, allow the reconstituted solution to stand for 5 to 10 minutes. The reconstituted preparation results in a colorless to slightly yellow, clear to slightly opalescent solution. Parenteral drug products should be inspected visually for particulate matter and discoloration prior to administration, whenever solution and container permit. Discard the solution if any particulate matter or discoloration is observed.

Dilution

- Once the reconstitution is completed, withdraw the necessary volume for the calculated dose from each vial, up to a maximum of 16 mL from 400 mg vial and 12 mL from 300 mg vial.
- Further dilute with either 0.9% Sodium Chloride Injection, USP or 5% Dextrose Injection, USP, into an infusion bag made of polyvinyl chloride or polyolefin. The final infusion concentration should range between 1 mg/mL and 6 mg/mL.
- The volume of 0.9% Sodium Chloride Injection, USP or 5% Dextrose Injection, USP should be adjusted so as not to exceed 5 mL/kg of patient weight at any given dose of EMPLICITI.

Complete the EMPLICITI infusion within 24 hours of reconstitution of the EMPLICITI lyophilized powder. If not used immediately, the infusion solution may be stored under refrigeration conditions: 2°C to 8°C (36°F-46°F) and protected from light for up to 24 hours (a maximum of 8 hours of the total 24 hours can be at room temperature, 20°C to 25°C [68°F-77°F], and room light).

3 DOSAGE FORMS AND STRENGTHS

For injection: 300 mg or 400 mg of elotuzumab as a white to off-white lyophilized powder in a single-dose vial for reconstitution.

4 CONTRAINDICATIONS

None.

5 WARNINGS AND PRECAUTIONS

5.1 Infusion Reactions

EMPLICITI can cause infusion reactions. Infusion reactions were reported in 10% of patients treated with EMPLICITI in the ELOQUENT-2 trial and 3.3% in the ELOQUENT-3 trial. In the ELOQUENT-2 trial, all reports of infusion reaction were Grade 3 or lower. In the ELOQUENT-2 trial, Grade 3 infusion reactions occurred in 1% of patients. The most common symptoms of an infusion reaction included fever, chills, and hypertension. Bradycardia and hypotension also developed during infusions.

In the ELOQUENT-2 trial, 5% of patients required interruption of the administration of EMPLICITI for a median of 25 minutes due to infusion reactions, and 1% of patients discontinued due to infusion reactions. Of the patients who experienced an infusion reaction, 70% (23/33) had them during the first dose.

In the ELOQUENT-3 trial, the only infusion reaction symptom was chest discomfort (2%), which was Grade 1. All patients in the ELOQUENT-3 trial who experienced an infusion reaction had them during the first treatment cycle.

Administer premedication consisting of dexamethasone, antihistamines (H1 and H2 blockers) and acetaminophen prior to EMPLICITI infusion [see Dosage and Administration (2.3)].

Interrupt EMPLICITI infusion for Grade 2 or higher infusion reactions and institute appropriate medical management [see Dosage and Administration (2.4)].

5.2 Infections

In the ELOQUENT-2 trial (N=635), infections were reported in 81% of patients in EMPLICITI combined with lenalidomide and dexamethasone (E-Ld) arm and 74% in lenalidomide and dexamethasone (Ld). In the ELOQUENT-3 trial (N=115), infections were reported in 65% of patients in both EMPLICITI combined with pomalidomide and dexamethasone (E-Pd) arm and in pomalidomide and dexamethasone (Pd) arm. In the ELOQUENT-2 trial, Grade 3 to 4 infections were noted in 28% and 24% of E-Ld- and Ld-treated patients and in the ELOQUENT-3 trial, 13% and 22% of E-Pd- and Pd-treated patients, respectively. Discontinuations due to infections occurred in 3.5% of E-Ld-treated and 4.1% of Ld-treated patients in the ELOQUENT-2 trial and 7% of E-Pd-treated and 5% of Pd-treated patients in the ELOQUENT-3 trial. Fatal infections were reported in 2.5% and 2.2% of E-Ld- and Ld-treated patients in the ELOQUENT-2 trial and 5% and 3.6% of E-Pd- and Pd-treated patients in the ELOQUENT-3 trial.

Opportunistic infections were reported in 22% of patients in the E-Ld arm and 13% of patients in the Ld arm in the ELOQUENT-2 trial and 10% of patients in the E-Pd arm and 9% of patients in the Pd arm in the ELOQUENT-3 trial. In the ELOQUENT-2 trial, fungal infections occurred in 10% of patients in the E-Ld arm and 5% of patients in the Ld arm. Herpes zoster was reported in 14% of patients treated with E-Ld and 7% of patients treated with Ld in the ELOQUENT-2 trial and 5% of patients treated with E-Pd and 1.8% of patients treated with Pd in the ELOQUENT-3 trial.

Monitor patients for development of infections and treat promptly.

5.3 Second Primary Malignancies

In the ELOQUENT-2 trial (N=635), invasive second primary malignancies (SPM) have been observed in 9% of patients treated with E-Ld and 6% of patients treated with Ld and in the ELOQUENT-3 trial (N=115) in 1.8% of patients treated with Pd and in none of the patients treated with E-Pd. In the ELOQUENT-2 trial, the rate of hematologic malignancies were the same between E-Ld and Ld treatment arms (1.6%). Solid tumors were reported in 3.5% and 2.2% of E-Ld- and Ld-treated patients, respectively. Skin cancer was reported in 4.4% and 2.8% of patients treated with E-Ld and Ld, respectively.

Monitor patients for the development of second primary malignancies.

5.4 Hepatotoxicity

In the ELOQUENT-2 trial (N=635), elevations in liver enzymes (aspartate transaminase/alanine transaminase [AST/ALT] greater than 3 times the upper limit, total bilirubin greater than 2 times the upper limit, and alkaline phosphatase less than 2 times the upper limit) consistent with hepatotoxicity were reported in 2.5% and 0.6% of E-Ld- and Ld-treated patients. Two patients experiencing hepatotoxicity were not able to continue treatment; however, 6 out of 8 patients had resolution and were able to continue treatment. Monitor liver enzymes periodically. Stop EMPLICITI upon Grade 3 or higher elevation of liver enzymes. After return to baseline values, continuation of treatment may be considered.

5.5 Interference with Determination of Complete Response

EMPLICITI is a humanized IgG kappa monoclonal antibody that can be detected on both the serum protein electrophoresis (SPEP) and immunofixation (IFE) assays used for the clinical monitoring of endogenous M-protein [see Drug Interactions (7.2)]. This interference can impact the determination of complete response and possibly relapse from complete response in patients with IgG kappa myeloma protein.

6 ADVERSE REACTIONS

The following clinically significant adverse reactions are described in detail in other sections of the label:

- Infusion reaction [see Warnings and Precautions (5.1)].
- Infections [see Warnings and Precautions (5.2)].
- Second Primary Malignancies [see Warnings and Precautions (5.3)].
- Hepatotoxicity [see Warnings and Precautions (5.4)].
- Interference with determination of complete response [see Warnings and Precautions (5.5)].

6.1 Clinical Trials Experience

Because clinical trials are conducted under widely varying conditions, adverse reaction rates observed in the clinical trials of a drug cannot be directly compared to rates in the clinical trials of another drug and may not reflect the rates observed in practice.

EMPLICITI in Combination with Lenalidomide and Dexamethasone [ELOQUENT-2]

The safety data described in this section are based on the ELOQUENT-2 study, a randomized, open-label clinical trial in patients with previously treated multiple myeloma. In ELOQUENT-2, EMPLICITI 10 mg/kg was administered with lenalidomide and dexamethasone [see Clinical Studies (14)]. For adverse reaction evaluation, EMPLICITI combined with lenalidomide and dexamethasone was compared with lenalidomide and dexamethasone alone.

The mean age of the population was 66 years and 57% of patients were 65 years of age or older. Sixty percent (60%) of the population were male, 84% were white, 10% were Asian, and 4% were black. The Eastern Cooperative Oncology Group (ECOG) performance status was 0 in 47%, 1 in 44%, and 2 in 9% of patients.

These data reflect exposure of 318 patients to EMPLICITI and 317 to control with a median number of cycles of 19 for EMPLICITI and 14 for control.

Serious adverse reactions were reported in 65% of patients treated on the EMPLICITI arm and 57% for patients treated on the control arm. The most frequent serious adverse reactions in the EMPLICITI arm compared to the control arm were: pneumonia (15% vs. 11%), pyrexia (7% vs. 5%), respiratory tract infection (3.1% vs. 1.3%), anemia (2.8% vs. 1.9%), pulmonary embolism (3.1% vs. 2.5%), and acute renal failure (2.5% vs. 1.9%).

The proportion of patients who discontinued any component of the treatment regimen due to adverse reactions as listed below was similar for both treatment arms; 6.0% for patients treated on the EMPLICITI arm and 6.3% for patients treated on the control.

Adverse reactions occurring at a frequency of 10% or higher in the EMPLICITI arm and 5% or higher than the lenalidomide and dexamethasone arm for the randomized trial in multiple myeloma are presented in Table 6.

Table 6: ELOQUENT-2: Adverse Reactions with a 10% or Higher Incidence for EMPLICITI-Treated Patients and a 5% or Higher Incidence than Lenalidomide and Dexamethasone-Treated Patients [All Grades]
 | EMPLICITI + Lenalidomide and Dexamethasone N=318 |  | Lenalidomide and Dexamethasone N=317
Primary Term | All Grades | Grade 3/4 | All Grades | Grade 3/4
Fatigue* | 62 | 13 | 52 | 12
Diarrhea | 47 | 5.0 | 36 | 4.1
Pyrexia | 37 | 2.5 | 25 | 2.8
Constipation | 36 | 1.3 | 27 | 0.3
Cough† | 34 | 0.3 | 19 | 0
Peripheral Neuropathy‡ | 27 | 3.8 | 21 | 2.2
Nasopharyngitis | 25 | 0 | 19 | 0
Upper Respiratory Tract Infection | 23 | 0.6 | 17 | 1.3
Decreased Appetite | 21 | 1.6 | 13 | 1.3
Pneumonia§ | 20 | 14 | 14 | 9
Pain in Extremities | 16 | 0.9 | 10 | 0.3
Headache | 15 | 0.3 | 8 | 0.3
Vomiting | 14 | 0.3 | 9 | 0.9
Weight Decreased | 14 | 1.3 | 6 | 0
Lymphopenia | 13 | 9 | 7 | 3.2
Cataracts | 12 | 6 | 6 | 2.8
Oropharyngeal Pain | 10 | 0 | 4 | 0
* The term fatigue is a grouping of the following terms: fatigue and asthenia.
† The term cough is a grouping of the following terms: cough, productive cough, and upper airway cough.
‡ The term peripheral neuropathy is a grouping of the following terms: peripheral neuropathy, axonal neuropathy, peripheral motor neuropathy, peripheral sensory neuropathy, and polyneuropathy.
§ The term pneumonia is a grouping of the following terms: pneumonia, atypical pneumonia, bronchopneumonia, lobar pneumonia, bacterial pneumonia, fungal pneumonia, pneumonia influenza, and pneumococcal pneumonia.

Laboratory abnormalities worsening from baseline and occurring at a frequency of 10% or higher in the EMPLICITI group and 5% or higher than the lenalidomide and dexamethasone group (criteria met for all Grades or Grade 3/4) for ELOQUENT-2 are presented in Table 7.

Table 7: ELOQUENT-2: Laboratory Abnormalities Worsening from Baseline and with a 10% or Higher Incidence for EMPLICITI-Treated Patients and a 5% Higher Incidence than Lenalidomide and Dexamethasone-Treated Patients [Criteria met for All Grades or Grade 3/4]
 | EMPLICITI + Lenalidomide and Dexamethasone N=318 |  | Lenalidomide and Dexamethasone N=317
Laboratory Parameter | All Grades | Grade 3/4 | All Grades | Grade 3/4
Hematology
Lymphopenia | 99 | 77 | 98 | 49
Leukopenia | 91 | 32 | 88 | 26
Thrombocytopenia | 84 | 19 | 78 | 20
Liver and Renal Function Tests
Hypoalbuminemia | 73 | 3.9 | 66 | 2.3
Elevated Alkaline Phosphatase | 39 | 1.3 | 30 | 0
Chemistry
Hyperglycemia | 89 | 17 | 85 | 10
Hypocalcemia | 78 | 11 | 77 | 4.7
Low Bicarbonate | 63 | 0.4 | 45 | 0
Hyperkalemia | 32 | 7 | 22 | 1.6

Vital sign abnormalities were assessed by treatment arm for the randomized trial in multiple myeloma and are presented in Table 8. Percentages are based on patients who had at least one vital sign abnormality any time during the course of study.

Table 8: ELOQUENT-2 Vital Sign Abnormalities
 | EMPLICITI + Lenalidomide and Dexamethasone N=318 | Lenalidomide and Dexamethasone N=317
Vital Sign Parameter | % | %
Systolic Blood Pressure ≥160 mmHg | 33 | 21
Diastolic Blood Pressure ≥100 mmHg | 17 | 12
Systolic Blood Pressure <90 mmHg | 29 | 8
Heart Rate ≥100 bpm | 48 | 30
Heart Rate <60 bpm | 66 | 31

EMPLICITI in Combination with Pomalidomide and Dexamethasone [ELOQUENT-3]

The safety data described in this section are based on ELOQUENT-3, a randomized, open-label clinical trial in patients with previously treated multiple myeloma. In ELOQUENT-3, EMPLICITI 10 mg/kg and 20 mg/kg was administered with pomalidomide and dexamethasone [see Clinical Studies (14)]. For adverse reaction evaluation, EMPLICITI combined with pomalidomide and dexamethasone was compared with pomalidomide and dexamethasone alone.

The mean age of the population was 66 years and 63% of patients were 65 years of age or older. Fifty-seven percent of the population were male, 78% were white, 20% were Asian, and none were black. The ECOG performance status was 0 in 43%, 1 in 46%, and 2 in 10% of patients. These data reflect exposure of 60 patients to EMPLICITI and 55 to control with a median number of cycles of 9 for EMPLICITI and 5 for control.

Serious adverse reactions were reported in 70% of patients treated on the EMPLICITI arm and 60% for patients treated on the control arm. The most frequent serious adverse reactions in the EMPLICITI arm compared to the control arm were: pneumonia (13% vs. 11%) and respiratory tract infection (7% vs. 3.6%). The proportion of patients who discontinued any component of the treatment regimen due to adverse reactions were 5% of the patients in the EMPLICITI arm and 1.8% of the patients in the control arm.

Adverse reactions occurring at a frequency of 10% or higher in the EMPLICITI arm and 5% or higher than the pomalidomide and dexamethasone arm for the randomized trial in multiple myeloma are presented in Table 9.

Table 9: ELOQUENT-3: Adverse Reactions with a 10% or Higher Incidence for EMPLICITI-Treated Patients and a 5% or Higher Incidence than Pomalidomide and Dexamethasone-Treated Patients [All Grades]
 | EMPLICITI + Pomalidomide and Dexamethasone N=60 |  | Pomalidomide and Dexamethasone N=55
Adverse Reaction | All Grades | Grade 3/4 | All Grades | Grade 3/4
Constipation | 22 | 1.7 | 11 | 0
Hyperglycemia | 20 | 8 | 15 | 7
Pneumonia* | 18 | 10 | 13 | 11
Diarrhea | 18 | 0 | 9 | 0
Respiratory Tract Infection | 17 | 0 | 9 | 1.8
Bone Pain | 15 | 3.3 | 9 | 0
Dyspnea | 15 | 3.3 | 7 | 1.8
Muscle Spasms | 13 | 0 | 5 | 0
Edema Peripheral | 13 | 0 | 7 | 0
Lymphopenia | 10 | 8 | 1.8 | 1.8
* The term pneumonia is grouping of the following terms: pneumonia, atypical pneumonia, lower respiratory tract infection, pneumoccocal sepsis, pneumonia bacterial, pneumonia influenza.

Other clinically important adverse reactions reported in patients treated with EMPLICITI that did not meet the criteria for inclusion in Table 6 and 9 but occurred at a frequency of 5% or greater in the EMPLICITI group and at a frequency at least twice the control rate for the randomized trial in multiple myeloma are listed below:

General disorders and administration site conditions: chest pain, night sweats

Immune system disorders: hypersensitivity

Nervous system disorders: hypoesthesia

Psychiatric disorders: mood altered

Laboratory abnormalities worsening from baseline and occurring at a frequency of 10% or higher in ELOQUENT-3 in the EMPLICITI group and 5% or higher than the pomalidomide and dexamethasone group (criteria met for all Grades or Grade 3/4) for the randomized trial in multiple myeloma are presented in Table 10.

Table 10: ELOQUENT-3: Laboratory Abnormalities Worsening from Baseline and with a 10% or Higher Incidence for EMPLICITI-Treated Patients and a 5% Higher Incidence than Pomalidomide and Dexamethasone-Treated Patients [Criteria met for All Grades or Grade 3/4]
 | EMPLICITI + Pomalidomide and Dexamethasone N=60 |  | Pomalidomide and Dexamethasone N=55
Laboratory Parameter | All Grades | Grade 3/4 | All Grades | Grade 3/4
Hematology
Lymphopenia | 98 | 70 | 91 | 35
Leukopenia | 80 | 52 | 87 | 35
Thrombocytopenia | 78 | 17 | 73 | 20
Liver and Renal Function Tests
Hypoalbuminemia | 65 | 1.7 | 56 | 1.8
Chemistry
Hypocalcemia | 58 | 3.3 | 40 | 1.8
Hyperglycemia | 40 | 3.3 | 25 | 1.8
Hyponatremia | 40 | 5 | 18 | 0
Hypokalemia | 23 | 5 | 16 | 3.6

Vital sign abnormalities were assessed by treatment arm for the randomized trial in multiple myeloma and are presented in Table 11. Percentages are based on all treated patients

Table 11: ELOQUENT-3: Vital Sign Abnormalities
 | EMPLICITI + Pomalidomide and Dexamethasone N=60 | Pomalidomide and Dexamethasone N=55
Vital Sign Parameter | % | %
Systolic Blood Pressure ≥160 mmHg | 18 | 13
Diastolic Blood Pressure ≥100 mmHg | 8 | 4.0
Systolic Blood Pressure <90 mmHg | 7 | 7
Heart Rate ≥100 bpm | 23 | 24
Heart Rate <60 bpm | 43 | 22

6.2 Immunogenicity

As with all therapeutic proteins, there is a potential for immunogenicity to EMPLICITI. The detection of antibody formation is highly dependent on the sensitivity and specificity of the assay. Additionally, the observed incidence of antibody (including neutralizing antibody) positivity in an assay may be influenced by several factors including assay methodology, sample handling, timing of sample collection, concomitant medications, and underlying disease. For these reasons, comparison of incidence of antibodies to EMPLICITI in the studies described below with the incidences of antibodies in other studies or to other products may be misleading.

Of 390 patients across four clinical studies including ELOQUENT-2 and in 53 patients in the ELOQUENT-3 trial, who were treated with EMPLICITI and evaluable for the presence of anti-product antibodies, 72 patients (18.5%) in the four clinical trials and 19 patients (36%) in the ELOQUENT-3 trial tested positive for treatment-emergent anti-product antibodies by an electrochemiluminescent (ECL) assay. In 63 (88%) of the 72 patients in the four clinical trials, anti-product antibodies occurred within the first 2 months of the initiation of EMPLICITI treatment and resolved by 2 to 4 months in 49 (78%) patients. In the ELOQUENT-3 trial, in all 19 patients, anti-product antibodies occurred within the first 2 months of the initiation of EMPLICITI treatment and were resolved by 2 to 3 months in 18 (95%) patients.

Neutralizing antibodies post-treatment were detected in 19 of 299 patients in the four clinical trials and 2 of 53 patients in the ELOQUENT-3 trial who were evaluable for the presence of neutralizing antibodies.

7 DRUG INTERACTIONS

7.1 Drug Interactions

For important drug interactions involving lenalidomide, pomalidomide and dexamethasone, refer to their respective prescribing information.

7.2 Laboratory Test Interference

EMPLICITI may be detected in the SPEP and serum immunofixation assays of myeloma patients and could interfere with correct response classification. A small peak in the early gamma region on SPEP that is IgGƙ on serum immunofixation may potentially be attributed to EMPLICITI, particularly in patients whose endogenous myeloma protein is IgA, IgM, IgD, or lambda light chain restricted. This interference can impact the determination of complete response and possibly relapse from complete response in patients with IgG kappa myeloma protein [see Warnings and Precautions (5.5)].

8 USE IN SPECIFIC POPULATIONS

8.1 Pregnancy

Risk Summary

There are no available data on EMPLICITI use in pregnant women to inform a drug associated risk of major birth defects and miscarriage. Animal reproduction studies have not been conducted with elotuzumab.

EMPLICITI is administered in combination with lenalidomide and dexamethasone or pomalidomide and dexamethasone. Lenalidomide and pomalidomide can cause embryo-fetal harm and are contraindicated for use in pregnancy. Refer to the lenalidomide, pomalidomide and dexamethasone prescribing information for additional information. Lenalidomide and pomalidomide are only available through a REMS program.

The background risk of major birth defects and miscarriage for the indicated population is unknown. All pregnancies have a background risk of birth defect, loss, or other adverse outcomes. In the U.S. general population, the estimated background risk of major birth defects and miscarriage in clinically recognized pregnancies is 2-4% and 15-20%, respectively.

8.2 Lactation

Risk Summary

There are no data on the presence of EMPLICITI in human milk, the effects on the breastfed child, or the effects on milk production. Because of the potential for serious adverse reactions in the breastfed child from elotuzumab administered in combination with lenalidomide and dexamethasone or pomalidomide and dexamethasone, advise lactating women not to breastfeed during treatment with EMPLICITI. Refer to the lenalidomide, pomalidomide and dexamethasone prescribing information for additional information.

8.3 Females and Males of Reproductive Potential

Pregnancy Testing

Refer to the lenalidomide and pomalidomide labeling for pregnancy testing requirements prior to initiating treatment in females of reproductive potential.

When EMPLICITI is used with lenalidomide or pomalidomide, there is a risk of fetal harm, including severe life-threatening human birth defects associated with lenalidomide and pomalidomide, and the need to follow requirements regarding pregnancy avoidance, including testing.

Contraception

Females

Refer to the lenalidomide and pomalidomide labeling for contraception requirements prior to initiating treatment in females of reproductive potential.

Males

Lenalidomide and pomalidomide are present in the blood and semen of patients receiving the drug. Refer to the lenalidomide and pomalidomide full prescribing information for requirements regarding contraception and the prohibitions against blood and/or sperm donation due to presence and transmission in blood and/or semen and for additional information.

8.4 Pediatric Use

Safety and effectiveness have not been established in pediatric patients.

8.5 Geriatric Use

Of the 646 patients across treatment groups in the ELOQUENT-2 randomized trial designed to evaluate the use of EMPLICITI in combination with lenalidomide and low-dose dexamethasone in multiple myeloma, 57% were 65 years of age or older; the number of patients 65 years or older was similar between treatment groups. No overall differences in efficacy or safety were observed between patients 65 years or older and younger patients (less than 65 years of age).

Of the 117 patients across treatment groups in the ELOQUENT-3 randomized trial designed to evaluate the use of EMPLICITI in combination with pomalidomide and low-dose dexamethasone in multiple myeloma, 62% were 65 years of age or older; the number of patients 65 years or older was similar between treatment groups. This study did not include sufficient numbers of subjects aged 65 and over to determine whether they respond differently from younger subjects.

10 OVERDOSAGE

The dose of EMPLICITI at which severe toxicity occurs is not known. EMPLICITI does not appear to be removed by dialysis as determined in a study of patients with renal impairment.

In case of overdosage, monitor patients closely for signs or symptoms of adverse reactions and institute appropriate symptomatic treatment.

11 DESCRIPTION

Elotuzumab is a humanized recombinant monoclonal antibody directed to SLAMF7, a cell surface glycoprotein. Elotuzumab consists of the complementary determining regions (CDR) of the mouse antibody, MuLuc63, grafted onto human IgG1 heavy and kappa light chain frameworks. Elotuzumab is produced in NS0 cells by recombinant DNA technology. Elotuzumab has a theoretical mass of 148.1 kDa for the intact antibody.

EMPLICITI (elotuzumab) is a sterile, nonpyrogenic, preservative-free lyophilized powder that is white to off-white, whole or fragmented cake in single-dose vials. EMPLICITI for Injection is supplied as 300 mg per vial and 400 mg per vial and requires reconstitution with Sterile Water for Injection, USP (13 mL and 17 mL, respectively) to obtain a solution with a concentration of 25 mg/mL. After reconstitution, each vial contains overfill to allow for withdrawal of 12 mL (300 mg) and 16 mL (400 mg). The reconstituted solution is colorless to slightly yellow, clear to slightly opalescent. Prior to intravenous infusion, the reconstituted solution is diluted with either 0.9% Sodium Chloride Injection, USP or 5% Dextrose Injection, USP [see Dosage and Administration (2.6)].

Each 300 mg single-dose vial of EMPLICITI also contains the following inactive ingredients: citric acid monohydrate (2.44 mg), polysorbate 80 (3.4 mg), sodium citrate (16.6 mg), and sucrose (510 mg).

Each 400 mg single-dose vial of EMPLICITI also contains the following inactive ingredients: citric acid monohydrate (3.17 mg), polysorbate 80 (4.4 mg), sodium citrate (21.5 mg), and sucrose (660 mg).

12 CLINICAL PHARMACOLOGY

12.1 Mechanism of Action

Elotuzumab is a humanized IgG1 monoclonal antibody that specifically targets the SLAMF7 (Signaling Lymphocytic Activation Molecule Family member 7) protein. SLAMF7 is expressed on myeloma cells independent of cytogenetic abnormalities. SLAMF7 is also expressed on Natural Killer (NK) cells, plasma cells, and at lower levels on specific immune cell subsets of differentiated cells within the hematopoietic lineage.

Elotuzumab directly activates NK cells through the SLAMF7 pathway. Elotuzumab also targets SLAMF7 on myeloma cells and interacts with Fc receptors on effector cells to mediate the killing of myeloma cells through antibody-dependent cellular cytotoxicity (ADCC) and antibody-dependent cellular phagocytosis (ADCP). In nonclinical models, the combination of elotuzumab and lenalidomide resulted in enhanced activation of NK cells that was greater than the effects of either agent alone and increased anti-tumor activity in vitro and in vivo. Elotuzumab has also demonstrated increased anti-tumor activity when combined with pomalidomide in vivo.

12.2 Pharmacodynamics

Cardiac Electrophysiology

EMPLICITI does not prolong the QT interval to any clinically relevant extent when administered with lenalidomide and dexamethasone at the recommended dose or as monotherapy (at a dose 2 times the recommended dose).

12.3 Pharmacokinetics

Elotuzumab exhibits nonlinear pharmacokinetics (PK) resulting in greater than proportional increases in area under the concentration-time curve (AUC) indicative of target-mediated clearance. The administration of the recommended 10 mg/kg EMPLICITI regimen with lenalidomide and dexamethasone is predicted to result in geometric mean (CV%) steady-state trough concentrations of 194 μg/mL (52%). The administration of the recommended EMPLICITI regimen with pomalidomide and dexamethasone is predicted to result in geometric mean (CV%) steady-state trough concentrations of 124 μg/mL (59%).

Elimination

The clearance of elotuzumab in combination with lenalidomide and dexamethasone decreased from a geometric mean (CV%) of 17.5 (21.2%) to 5.8 (31%) mL/day/kg with an increase in dose from 0.5 (i.e., 0.05 times the recommended dosage) to 20 mg/kg (i.e., 2 times the recommended dosage). When elotuzumab is administered with lenalidomide and dexamethasone, approximately 97% of the maximum steady-state concentration is predicted to be eliminated with a geometric mean (CV%) of 82.4 (48%) days. When elotuzumab is administered with pomalidomide and dexamethasone, approximately 97% of the maximum steady-state concentration is predicted to be eliminated with a geometric mean (CV%) of 78 (42%) days.

Specific Populations

Clinically significant differences were not observed in the PK of elotuzumab based on age (37 to 88 years), sex, race, baseline lactate dehydrogenase, albumin, renal impairment (creatinine clearance (CLcr) 15 to 89 mL/min), end-stage renal disease (CLcr <15 mL/min) with or without hemodialysis, mild hepatic impairment (total bilirubin ≤ upper limit of normal (ULN) and aspartate transaminase (AST) > ULN OR total bilirubin 1 to 1.5 times the ULN and AST any value), and coadministration with lenalidomide/dexamethasone or pomalidomide/dexamethasone. The PK of elotuzumab in patients with moderate (total bilirubin > 1.5 to 3 times the ULN and AST any value) to severe (total bilirubin > 3 times the ULN and AST any value) hepatic impairment is unknown.

The clearance of elotuzumab increased with increasing body weight supporting a weight-based dose.

13 NONCLINICAL TOXICOLOGY

13.1 Carcinogenesis, Mutagenesis, Impairment of Fertility

No carcinogenicity or mutagenicity data are available for elotuzumab in animals or humans. Fertility studies have not been performed for elotuzumab.

14 CLINICAL STUDIES

ELOQUENT-2 (NCT01239797)

The efficacy and safety of EMPLICITI in combination with lenalidomide and dexamethasone were evaluated in ELOQUENT-2, a randomized, open-label trial in patients with multiple myeloma who had received one to three prior therapies and had documented progression following their most recent therapy.

Eligible patients were randomized in a 1:1 ratio to receive either EMPLICITI in combination with lenalidomide and low-dose dexamethasone or lenalidomide and low-dose dexamethasone. Treatment was administered in 4-week cycles until disease progression or unacceptable toxicity. EMPLICITI 10 mg/kg was administered intravenously each week for the first 2 cycles and every 2 weeks thereafter. Prior to EMPLICITI infusion, dexamethasone was administered as a divided dose: an oral dose of 28 mg and an intravenous dose of 8 mg. In the control group and on weeks without EMPLICITI, dexamethasone 40 mg was administered as a single oral dose weekly. Lenalidomide 25 mg was taken orally once daily for the first 3 weeks of each cycle. Assessment of tumor response was conducted every 4 weeks.

A total of 646 patients were randomized to receive treatment: 321 to EMPLICITI in combination with lenalidomide and low-dose dexamethasone and 325 to lenalidomide and low-dose dexamethasone.

Demographics and baseline disease characteristics were balanced between treatment arms. The median age was 66 years (range, 37-91); 57% of patients were 65 years or older; 60% of patients were male; whites comprised 84% of the study population, Asians 10%, and blacks 4%. The ECOG performance status was 0 in 47%, 1 in 44%, and 2 in 9% of patients, and ISS Stage was I in 43%, II in 32%, and III in 21% of patients. The cytogenetic categories of del 17p and t(4;14) were present in 32% and 9% of patients, respectively. The median number of prior therapies was 2. Thirty-five percent (35%) of patients were refractory (progression during or within 60 days of last therapy) and 65% were relapsed (progression after 60 days of last therapy). Prior therapies included stem cell transplant (55%), bortezomib (70%), melphalan (65%), thalidomide (48%), and lenalidomide (6%).

The efficacy of EMPLICITI was evaluated by progression-free survival (PFS) as assessed by hazard ratio, and overall response rate (ORR) as determined by a blinded Independent Review Committee using the European Group for Blood and Marrow Transplantation (EBMT) response criteria. Efficacy results are shown in Table 12 and Figure 1. The median number of treatment cycles was 19 for the EMPLICITI group and 14 for the comparator arm with a minimum follow-up of two years.

A pre-planned final overall survival (OS) analysis was performed after at least 427 deaths occurred. The minimum follow-up was 70.6 months. The OS results at final analysis reached statistical significance. A significantly longer OS was observed in patients in the E-Ld arm compared to patients in Ld arm, representing an 18% reduction in the risk of death. Efficacy results are presented in Table 12 and Figure 2.

Table 12: ELOQUENT-2 Efficacy Results
 | EMPLICITI + Lenalidomide/ Dexamethasone N=321 | Lenalidomide/ Dexamethasone N=325
PFS
Hazard Ratio [95% CI] | 0.70 [0.57, 0.85]
Stratified log-rank test p-value* | 0.0004
Median PFS in months [95% CI] | 19.4 [16.6, 22.2] | 14.9 [12.1, 17.2]
Response
Overall Response (ORR)† n (%) [95% CI] | 252 (78.5) [73.6, 82.9] | 213 (65.5) [60.1, 70.7]
p-value‡ | 0.0002
Complete Response (CR + sCR)†,§ n (%) | 14 (4.4)¶ | 24 (7.4)
Very Good Partial Response (VGPR)† n (%) | 91 (28.3) | 67 (20.6)
Partial Response (PR)† n (%) | 147 (45.8) | 122 (37.5)
Overall Survival
Hazard Ratio [95.4% CI] | 0.82 [0.68, 1.00]
Stratified log-rank test p-value* | 0.0408
Median OS in months [95% CI] | 48.3 [40.3, 51.9] | 39.6 [33.3, 45.3]
* p-value based on the log-rank test stratified by ß2 microglobulins (<3.5 mg/L vs ≥3.5 mg/L), number of prior lines of therapy (1 vs 2 or 3), and prior immunomodulatory therapy (no vs prior thalidomide only vs other).
† European Group for Blood and Marrow Transplantation (EBMT) criteria.
‡ p-value based on the Cochran-Mantel-Haenszel chi-square test stratified by ß2 microglobulins (<3.5 mg/L vs ≥3.5 mg/L), number of prior lines of therapy (1 vs 2 or 3), and prior immunomodulatory therapy (no vs prior thalidomide only vs other).
§ Complete response (CR) + stringent complete response (sCR).
¶ EMPLICITI’s interference with the assessment of myeloma protein with immunofixation and serum protein electrophoresis assay may interfere with correct response classification [see Drug Interactions (7)].

Figure 1: ELOQUENT-2 Progression-Free Survival

The 1- and 2-year rates of PFS for EMPLICITI in combination with lenalidomide and dexamethasone treatment were 68% and 41%, respectively, compared with 57% and 27%, respectively, for lenalidomide and dexamethasone treatment.

Figure 2: ELOQUENT-2 Overall Survival

ELOQUENT-3 (NCT02654132)

The efficacy and safety of EMPLICITI in combination with pomalidomide and dexamethasone were evaluated in ELOQUENT-3, a randomized, open-label trial in patients with relapsed or refractory multiple myeloma.

Eligible patients were randomized in a 1:1 ratio to receive either EMPLICITI in combination with pomalidomide and low-dose dexamethasone or pomalidomide and low-dose dexamethasone. Treatment was administered in 4-week cycles until disease progression or unacceptable toxicity. EMPLICITI 10 mg/kg was administered intravenously each week for the first 2 cycles and 20 mg/kg every 4 weeks thereafter.

Prior to EMPLICITI infusion, dexamethasone was administered. Dexamethasone was administered on day 1, 8, 15 and 22 of each cycle. On weeks with EMPLICITI infusion, dexamethasone was administered as a divided dose: subjects 75 years or younger, an oral dose of 28 mg and an intravenous dose of 8 mg, and in subjects older than 75 years an oral dose of 8 mg and an intravenous dose of 8 mg. On weeks without an EMPLICITI infusion and in the control group, dexamethasone was administered in subjects 75 years or younger as an oral dose of 40 mg and in subjects older than 75 years as an oral dose of 20 mg dexamethasone was administered orally. Assessment of tumor response was conducted every 4 weeks.

A total of 117 patients were randomized to receive treatment: 60 to EMPLICITI in combination with pomalidomide and low-dose dexamethasone and 57 to pomalidomide and low-dose dexamethasone.

Demographics and baseline disease characteristics were balanced between treatment arms. The median age was 67 years (range, 36-81); 62% of patients were 65 years or older; 57% of patients were male; whites comprised 77% of the study population, Asians 21%, and blacks 1%. The ECOG performance status was 0 in 44%, 1 in 46%, and 2 in 10% of patients, and ISS Stage was I in 50%, II in 38%, and III in 12% of patients. The chromosomal lab abnormalities as determined by FISH of del 17p and t(4;14) were present in 5% and 11% of patients, respectively. The median number of prior therapies was 3. Eighty-seven percent (87%) of patients were refractory to lenalidomide, 80% refractory to a proteasome inhibitor, 70% were refractory to both lenalidomide and a proteasome inhibitor. Prior therapies included stem cell transplant (55%), bortezomib (100%), lenalidomide (99%), cyclophosphamide (66%), melphalan (63%), carfilzomib (21%), and daratumumab (3%).

The efficacy of EMPLICITI was evaluated by progression-free survival (PFS) and overall response rate (ORR) as determined by the investigator. Efficacy results are shown in Table 13 and Figure 3. The median number of treatment cycles was 9 for the EMPLICITI group and 5 for the comparator arm with a minimum follow-up of 9.1 months.

A pre-planned final OS analysis was performed after at least 78 deaths occurred. The minimum follow-up was 45.0 months. A longer OS was observed in patients in the E-Pd arm compared to patients in the Pd arm. Efficacy results are presented in Table 13 and Figure 4.

Table 13: ELOQUENT-3 Efficacy Results
 | EMPLICITI + Pomalidomide/ Dexamethasone N=60 | Pomalidomide/ Dexamethasone N=57
PFS
Hazard Ratio [95% CI] | 0.54 [0.34, 0.86]
Stratified log-rank test p-value* | 0.0078
Median PFS in months [95% CI] | 10.25 [5.59, NE] | 4.67 [2.83, 7.16]
Response
Overall Response (ORR)† n (%) [95% CI] | 32 (53.3) [40.0, 66.3] | 15 (26.3) [15.5, 39.7]
p-value‡ | 0.0029
Complete Response (CR + sCR)†,§ n (%) | 5 (8.3)¶ | 1 (1.8)
Very Good Partial Response (VGPR)† n (%) | 7 (11.7) | 4 (7.0)
Partial Response (PR)† n (%) | 20 (33.3) | 10 (17.5)
Overall Survival
Number of death events | 37 (61.7) | 41 (74.5)
Hazard Ratio [95% CI] | 0.59 [0.37, 0.93]
Median OS in months [95% CI] | 29.80 [22.87, 45.67] | 17.41 [13.83, 27.70]
* p-value based on the log-rank test stratified by stage of disease at study entry (International Staging System I-II vs III) and number of prior lines of therapy (2-3 vs >=4) at randomization.
† International Myeloma Working Group (IMWG) criteria.
‡ p-value based on the Cochran-Mantel-Haenszel chi-square test stratified by stage of disease at study entry (International Staging System I-II vs III) and number of prior lines of therapy (2-3 vs >=4) at randomization.
§ Complete response (CR) + stringent complete response (sCR).
¶ EMPLICITI’s interference with the assessment of myeloma protein with immunofixation and serum protein electrophoresis assay may interfere with correct response classification [see Drug Interactions (7)].
NE=Non-Estimable

Figure 3: ELOQUENT-3 Progression-Free Survival

Figure 4: ELOQUENT-3 Overall Survival

16 HOW SUPPLIED/STORAGE AND HANDLING

EMPLICITI (elotuzumab) is white to off-white lyophilized powder available as follows:

Carton Content | NDC
One 300 mg single-dose vial | 0003-2291-11
One 400 mg single-dose vial | 0003-4522-11

Store EMPLICITI under refrigeration at 2°C to 8°C (36°F-46°F). Protect EMPLICITI from light by storing in the original package until time of use. Do not freeze or shake.

17 PATIENT COUNSELING INFORMATION

Advise the patient to read the FDA-approved patient labeling (Patient Information).

Infusion Reactions

- EMPLICITI may cause infusion reactions. Advise patients to contact their healthcare provider if they experience signs and symptoms of infusion reactions, including fever, chills, rash, or breathing problems within 24 hours of infusion [see Warnings and Precautions (5.1)].
- Advise patients that they will be required to take the following oral medications prior to EMPLICITI dosing to reduce the risk of infusion reaction [see Dosage and Administration (2.3)]:
  - Dexamethasone orally as prescribed
  - H1 blocker: diphenhydramine or equivalent (if oral)
  - H2 blocker: ranitidine or equivalent (if oral)
  - Acetaminophen (650 to 1000 mg orally)

Pregnancy

- Advise patients that lenalidomide and pomalidomide have the potential to cause fetal harm and has specific requirements regarding contraception, pregnancy testing, blood and sperm donation, and transmission in sperm. Lenalidomide and pomalidomide are only available through a REMS program [see Use in Specific Populations (8.1)].

Infections

- Inform patients of the risk of developing infections during treatment with EMPLICITI, and to report any symptoms of infection [see Warnings and Precautions (5.2)].

Second Primary Malignancies

- Inform patients of the risk of developing SPM during treatment with EMPLICITI [see Warnings and Precautions (5.3)].

Hepatotoxicity

- Inform patients of the risk of hepatotoxicity during treatment with EMPLICITI and to report any signs and symptoms associated with this event to their healthcare provider for evaluation [see Warnings and Precautions (5.4)].
Manufactured by:
  Bristol-Myers Squibb Company
  Princeton, NJ 08543 USA
  U.S. License No. 1713

Patient Information

EMPLICITI® (em-plis-city)

(elotuzumab)

for injection

EMPLICITI is used with other prescription medicines called REVLIMID® (lenalidomide) and dexamethasone or POMALYST® (pomalidomide) and dexamethasone. Read the Medication Guide that comes with REVLIMID if used with REVLIMID and POMALYST if used with POMALYST. You can ask your healthcare provider or pharmacist for information about dexamethasone.

What is EMPLICITI?

EMPLICITI is a prescription medicine used to treat:

- multiple myeloma in combination with the medicines REVLIMID (lenalidomide) and dexamethasone in adults who have received one to three prior treatments for their multiple myeloma.
- multiple myeloma in combination with the medicines POMALYST (pomalidomide) and dexamethasone in adults who have received at least two prior treatments including REVLIMID (lenalidomide) and a proteasome inhibitor.

It is not known if EMPLICITI is safe and effective in children.

Before you receive EMPLICITI, tell your healthcare provider about all of your medical conditions, including if you:

- have an infection
- are pregnant or plan to become pregnant. It is not known if EMPLICITI may harm your unborn baby. However, REVLIMID and POMALYST may cause birth defects or death of an unborn baby.
  - Before receiving EMPLICITI with REVLIMID and dexamethasone, or EMPLICITI with POMALYST and dexamethasone, females and males must agree to the instructions in the REVLIMID REMS® program for the use of EMPLICITI in combination with REVLIMID and dexamethasone and the POMALYST REMS® program for the use of EMPLICITI in combination with POMALYST and dexamethasone.
  - The REVLIMID REMS and POMALYST REMS programs have specific requirements about birth control (contraception), pregnancy testing, blood donation, and sperm donation that you need to know. Talk to your healthcare provider to learn more about REVLIMID or POMALYST.
- are breastfeeding or plan to breastfeed. It is not known if EMPLICITI passes into breast milk. You should not breastfeed during treatment with EMPLICITI and REVLIMID and dexamethasone or EMPLICITI and POMALYST and dexamethasone.
- Tell your healthcare provider about all the medicines you take, including prescription and over-the-counter medicines, vitamins, and herbal supplements.

How will I receive EMPLICITI?

- EMPLICITI will be given to you by intravenous (IV) infusion into your vein.
- Your EMPLICITI treatment schedule is divided into cycles that are 28 days (4 weeks) long. A cycle includes the number of days you are on treatment and also the time you spend resting in between treatments.
- EMPLICITI with REVLIMID and dexamethasone is usually given as follows:
  - Cycles 1 and 2 (28 days per cycle), you will receive EMPLICITI one time every week.
  - Cycles 3 and up (28 days per cycle), you will receive EMPLICITI one time every 2 weeks.
- EMPLICITI with POMALYST and dexamethasone is usually given as follows:
  - Cycle 1 and 2 (28 days per cycle), you will receive EMPLICITI one time every week.
  - Cycle 3 and up (28 days per cycle), you will receive EMPLICITI one time every 4 weeks.
- Your healthcare provider will decide how many treatments you will receive.
- Before every EMPLICITI infusion, you will receive medicines to help reduce the risk of infusion reactions.
- If you miss any appointments call your healthcare provider as soon as possible.

What are the possible side effects of EMPLICITI?

EMPLICITI may cause serious side effects, including:

- Infusion reactions. Infusion reactions can happen during your infusion or within 24 hours after your infusion of EMPLICITI. Your healthcare provider will give you medicines before each infusion of EMPLICITI to help reduce the risk of an infusion reaction.
If you have an infusion reaction while receiving EMPLICITI, your healthcare provider will slow or stop your infusion and treat your reaction. If you have a severe infusion reaction, your healthcare provider may stop your treatment completely. Tell your healthcare provider or get medical help right away if you have any of these symptoms after your infusion with EMPLICITI:

- fever
- chills
- rash
- chest pain

- trouble breathing
- dizziness
- light-headedness

- Infections. People with multiple myeloma who receive EMPLICITI with REVLIMID and dexamethasone or EMPLICITI with POMALYST and dexamethasone may develop infections that can be serious. Tell your healthcare provider right away if you have any signs and symptoms of an infection, including:

- fever
- flu-like symptoms
- cough

- shortness of breath
- burning with urination
- a painful skin rash

- Risk of new cancers (malignancies). People with multiple myeloma who receive EMPLICITI with REVLIMID and dexamethasone or EMPLICITI with POMALYST and dexamethasone have a risk of developing new cancers. Talk with your healthcare provider about your risk of developing new cancers if you receive EMPLICITI. Your healthcare provider will check you for new cancers during your treatment with EMPLICITI.

- Liver problems. EMPLICITI may cause liver problems. Your healthcare provider will do blood tests to check your liver during treatment with EMPLICITI. Tell your healthcare provider if you have signs and symptoms of liver problems, including: tiredness, weakness, loss of appetite, yellowing of your skin or eyes, color changes in your stools, confusion, or swelling of the stomach area.

The most common side effects of EMPLICITI when used with REVLIMID and dexamethasone include:

- fatigue
- diarrhea
- fever
- constipation
- cough

- numbness, weakness, tingling, or burning pain in your arms or legs
- sore throat or runny nose
- upper respiratory tract infection
- decreased appetite
- pneumonia

The most common side effects of EMPLICITI when used with POMALYST and dexamethasone include:

- constipation
- high blood sugar

These are not all of the possible side effects of EMPLICITI.

Call your doctor for medical advice about side effects. You may report side effects to FDA at 1-800-FDA-1088.

You may also report side effects to Bristol-Myers Squibb at 1-800-721-5072.

General information about the safe and effective use of EMPLICITI

Medicines are sometimes prescribed for purposes other than those listed in a Patient Information leaflet.

You can ask your pharmacist or healthcare provider for information about EMPLICITI that is written for health professionals.

What are the ingredients of EMPLICITI?

Active ingredient: elotuzumab

Inactive ingredients: citric acid monohydrate, polysorbate 80, sodium citrate, sucrose

For more information, call 1-844-EMPLICITI (844-367-5424) or visit EMPLICITI.com.

EMPLICITI® is a trademark of Bristol-Myers Squibb Company. All other trademarks are the property of their respective owners.

Manufactured by: Bristol-Myers Squibb Company, Princeton, NJ 08543 USA

U.S. License No. 1713

This Patient Information has been approved by the U.S. Food and Drug Administration.

Revised: 3/2022

EMPLICITI 300 mg Representative Packaging

NDC 0003-2291-11
Rx only
Empliciti®
(elotuzumab)
for Injection
300 mg per vial
For intravenous Infusion Only
Reconstitute and Further Dilute Prior to Use
Single-Dose Vial. Discard Unused Portion.
Bristol-Myers Squibb

EMPLICITI 400 mg Representative Packaging

NDC 0003-4522-11
Rx only
Empliciti®
(elotuzumab)
for Injection
400 mg per vial
For intravenous Infusion Only
Reconstitute and Further Dilute Prior to Use
Single-Dose Vial. Discard Unused Portion.
Bristol-Myers Squibb